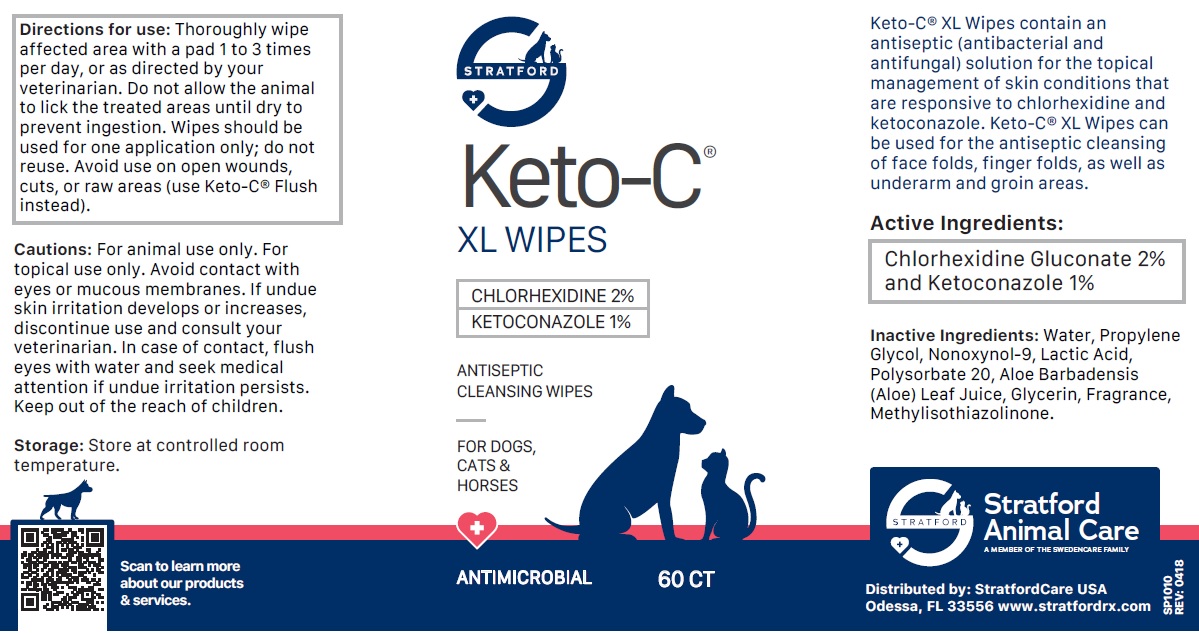 DRUG LABEL: Keto-C XL Wipes 60 count
NDC: 86069-115 | Form: CLOTH
Manufacturer: Stratford Care Usa, Inc.
Category: animal | Type: OTC ANIMAL DRUG LABEL
Date: 20221121

ACTIVE INGREDIENTS: CHLORHEXIDINE GLUCONATE 2 g/100 mL; KETOCONAZOLE 1 g/100 mL
INACTIVE INGREDIENTS: WATER; PROPYLENE GLYCOL; NONOXYNOL-9; LACTIC ACID, UNSPECIFIED FORM; POLYSORBATE 20; ALOE VERA LEAF; GLYCERIN; METHYLISOTHIAZOLINONE

Keto-C® XL WIPES

Active Ingredients:

Chlorhexidine Gluconate 2% and Ketoconazole 1%

PURPOSE

antibacterial and antifungal

INDICATIONS AND USAGE

Keto-C® XL Wipes contain an antiseptic (antibacterial and antifungal) solution for the topical management of skin conditions that are responsive to chlorhexidine and ketoconazole. Keto-C® XL Wipes can be used for the antiseptic cleansing of face folds, finger folds, as well as underarms and groin areas.

INACTIVE INGREDIENT

Inactive Ingredients: Water, Propylene Glycol, Nonoxynol-9, Lactic Acid, Polysorbate 20, Aloe Barbadensis (Aloe) Leaf Juice, Glycerin, Fragrance, Methylisothiazolinone.

DOSAGE AND ADMINISTRATION

Directions for use: Thoroughly wipe affected area with a pad 1 to 3 times per day, or as directed by your veterinarian. Do not allow the animal to lick the treated areas until dry to prevent ingestion. Wipes should be used for one application only; do not reuse. Avoid use on open wounds, cuts, or raw areas (use Keto-C® Flush instead).

PRECAUTIONS

Cautions: For animal use only. For topical use only. Avoid contact with eyes or mucous membranes. If undue skin irritation develops or increases, discontinue use and consult your veterinarian. In case of contact, flush eyes with water and seek medical attention if undue irritation persists. Keep out of the reach of children.

Storage: Store at controlled room temperature.

ANTISEPTIC CLEANSING WIPES

FOR DOGS, CATS & HORSES

ANTIMICROBIAL

Stratford Animal Care
A MEMBER OF THE SWEDENCARE FAMILY

Distributed by: StratfordCare USA
Odessa, FL 33556 www.stratfordrx.com